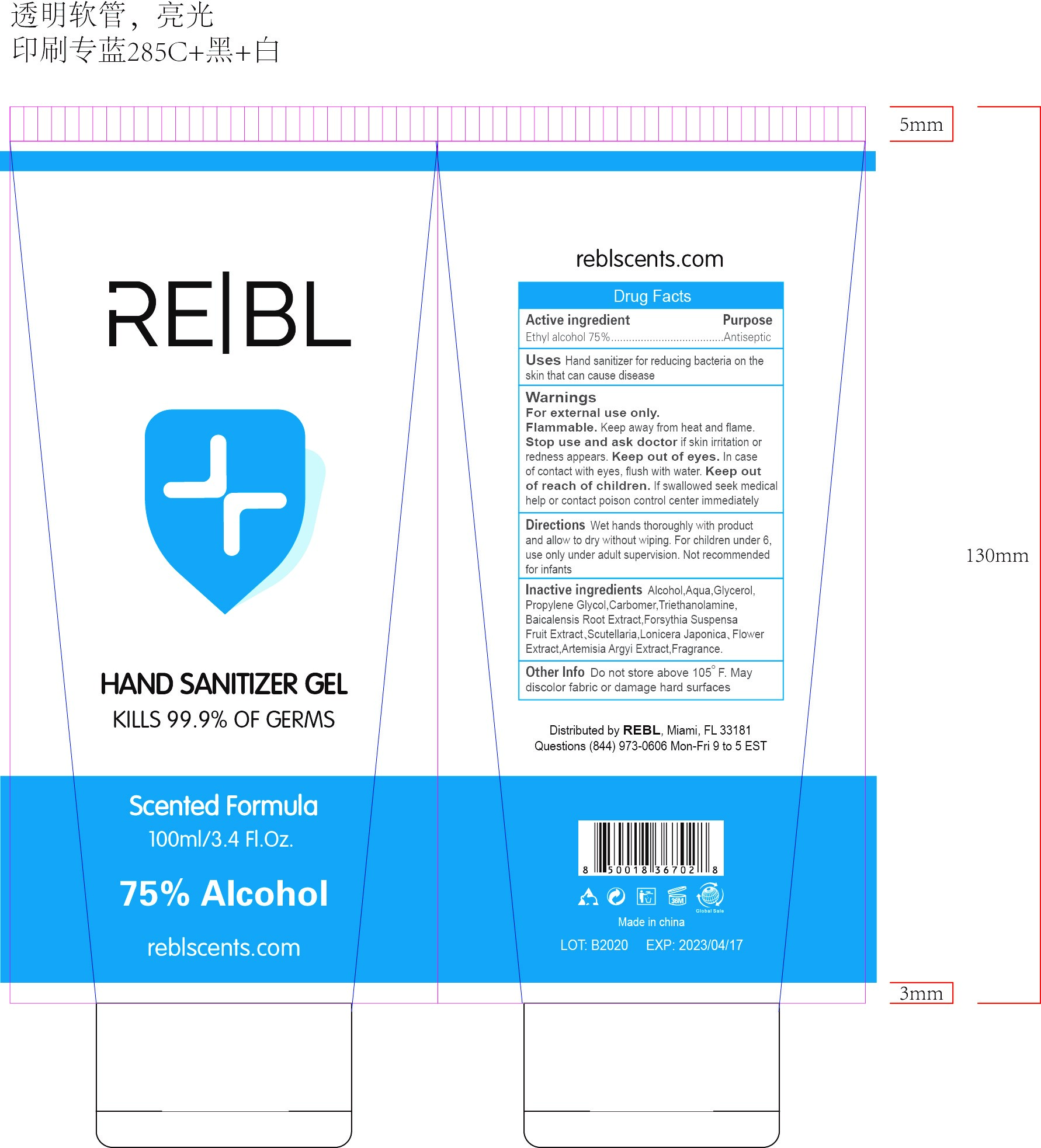 DRUG LABEL: HAND SANITIZER
NDC: 76888-001 | Form: GEL
Manufacturer: Guangdong Meishanlian Cosmetics Co.,Ltd
Category: otc | Type: HUMAN OTC DRUG LABEL
Date: 20200427

ACTIVE INGREDIENTS: ALCOHOL 75 mL/100 mL
INACTIVE INGREDIENTS: GLYCERIN 1.45 mL/100 mL; HYDROGEN PEROXIDE 0.125 mL/100 mL; WATER

HAND WASHING GEL

Active Ingredient(s)

Ethyl alcohol 75%. Purpose: Antiseptic

Purpose

Antiseptic, Hand Sanitizer

Use

Hand Sanitizer for reducing bacteria on the skin that can cause disease

Warnings

For external use only. Flammable. Keep away from heat or flame

When using this product keep out of eyes, ears, and mouth. In case of contact with eyes, rinse eyes thoroughly with water.
Stop use and ask a doctor if irritation or rash occurs. These may be signs of a serious condition.
Keep out of reach of children. If swallowed, get medical help or contact a Poison Control Center right away.

Stop use and ask a doctor if irritation or rash occurs. These may be signs of a serious condition.

Keep out of reach of children. If swallowed, get medical help or contact a Poison Control Center right away.

Directions

Wet hands thoroughly with product and allow to dry without wiping.For children under 6,use only under adult supervision.Not recommended for infants.

Other information

Do not store above 105℉,May discolor fabric or damage hard surface

Inactive ingredients

glycerin, hydrogen peroxide, purified water USP

Package Label - Principal Display Panel

100 mL NDC: 76888-001-01